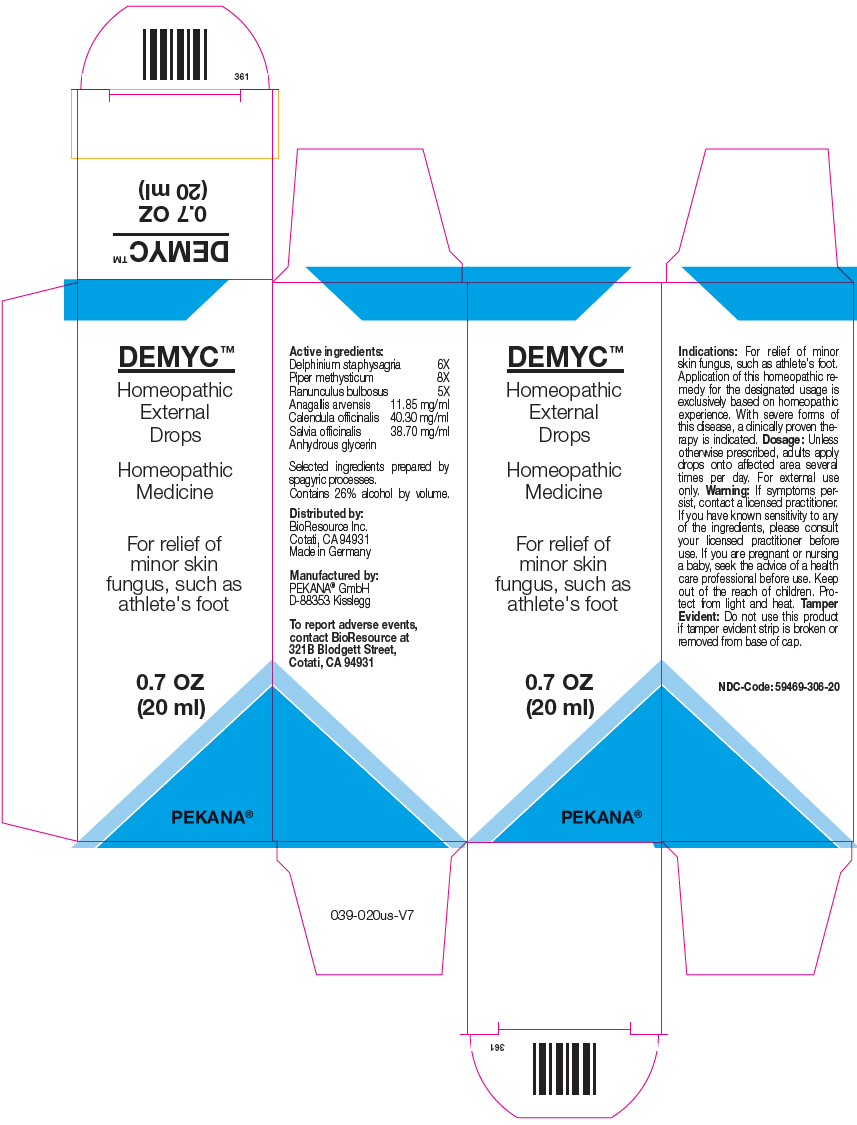 DRUG LABEL: DEMYC
NDC: 59469-306 | Form: SOLUTION/ DROPS
Manufacturer: PEKANA Naturheilmittel GmbH
Category: homeopathic | Type: HUMAN OTC DRUG LABEL
Date: 20230111

ACTIVE INGREDIENTS: RANUNCULUS BULBOSUS WHOLE 5 [hp_X]/20 mL; DELPHINIUM STAPHISAGRIA SEED 6 [hp_X]/20 mL; PIPER METHYSTICUM ROOT 8 [hp_X]/20 mL; LYSIMACHIA ARVENSIS WHOLE 237 mg/20 mL; CALENDULA OFFICINALIS FLOWERING TOP 806 mg/20 mL; SAGE 774 mg/20 mL
INACTIVE INGREDIENTS: GLYCERIN; WATER; ALCOHOL

DEMYC™

Active ingredients:
Delphinium staphysagria | 6X
Piper methysticum | 8X
Ranunculus bulbosus | 5X
Anagallis arvensis | 11.85 mg/ml
Calendula officinalis | 40.30 mg/ml
Salvia officinalis Anhydrous glycerin | 38.70 mg/ml

Selected ingredients prepared by spagyric processes.

INACTIVE INGREDIENT

Contains 26% alcohol by volume.

Indications

PURPOSE

For relief of minor skin fungus, such as athlete's foot. Application of this homeopathic remedy for the designated usage is exclusively based on homeopathic experience. With severe forms of this disease, a clinically proven therapy is indicated.

Dosage

Unless otherwise prescribed, adults apply drops onto affected area several times per day. For external use only.

Warning

If symptoms persist, contact a licensed practitioner. If you have known sensitivity to any of the ingredients, please consult your licensed practitioner before use. If you are pregnant or nursing a baby, seek the advice of a health care professional before use.

Keep out of the reach of children.

STORAGE AND HANDLING

Protect from light and heat.

Tamper Evident

Do not use this product if tamper evident strip is broken or removed from base of cap.

QUESTIONS

To report adverse events, contact BioResource at 321B Blodgett Street, Cotati, CA 94931

Distributed by:
BioResource Inc.
Cotati, CA 94931

Manufactured by:
PEKANA® GmbH
D-88353 Kisslegg

PRINCIPAL DISPLAY PANEL - 20 ml Bottle Box

DEMYC™

Homeopathic
External
Drops

Homeopathic
Medicine

For relief of
minor skin
fungus, such as
athlete's foot

0.7 OZ
(20 ml)

PEKANA®